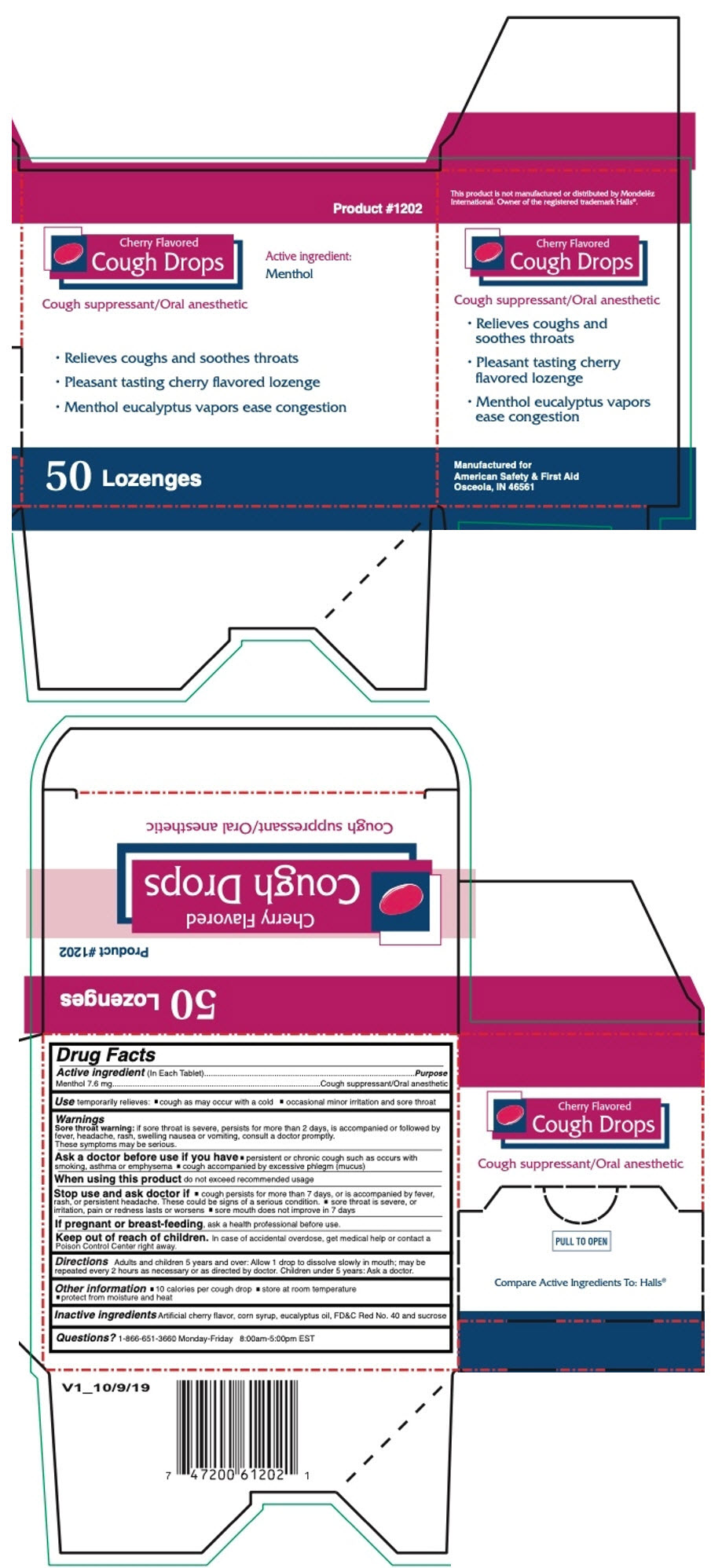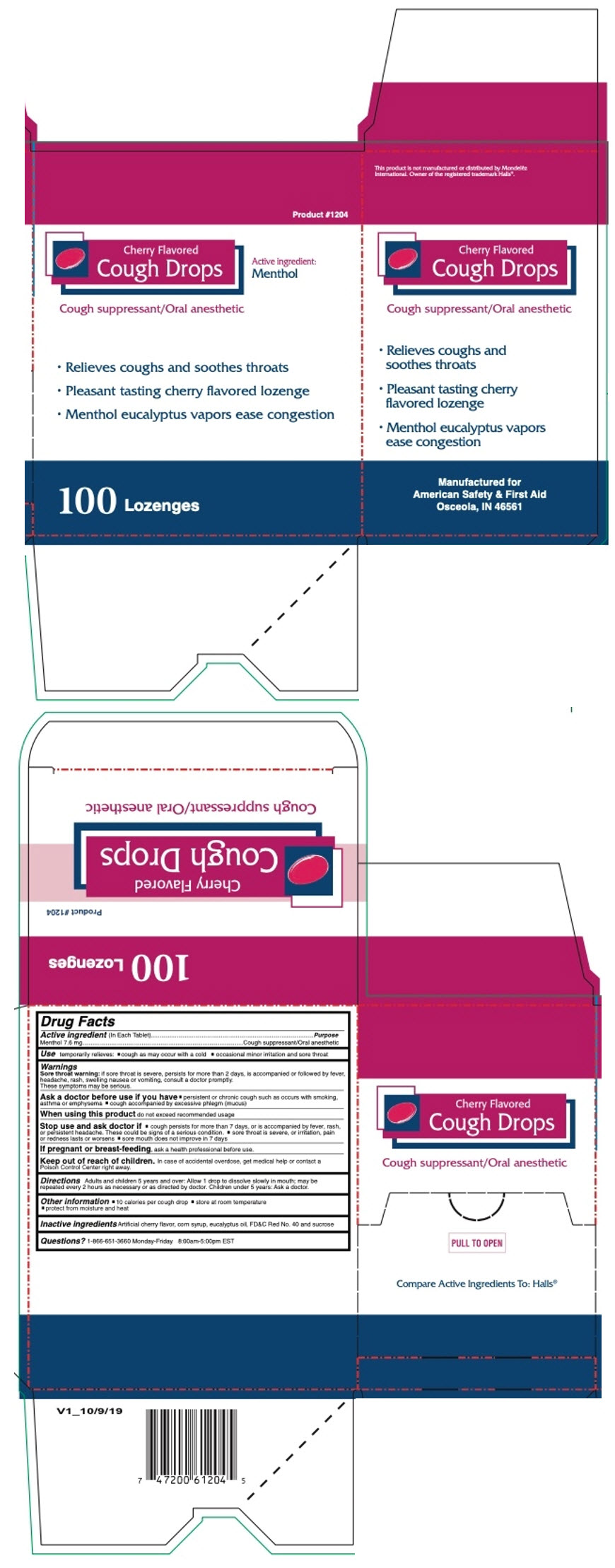 DRUG LABEL: CHERRY COUGH DROPS 50CT
NDC: 73598-1202 | Form: LOZENGE
Manufacturer: JHK Inc dba American Safety & First Aid
Category: otc | Type: HUMAN OTC DRUG LABEL
Date: 20240424

ACTIVE INGREDIENTS: MENTHOL, UNSPECIFIED FORM 7.6 mg/1 1
INACTIVE INGREDIENTS: CORN SYRUP; EUCALYPTUS OIL; FD&C RED NO. 40; SUCROSE

CHERRY COUGH DROPS

Drug Facts

Active ingredient (In Each Tablet)

Menthol 7.6 mg

Purpose

Cough suppressant/Oral anesthetic

Use

temporarily relieves:

- cough as may occur with a cold
- occasional minor irritation and sore throat

Warnings

Sore throat warning: if sore throat is severe, persists for more than 2 days, is accompanied or followed by fever, headache, rash, swelling nausea or vomiting, consult a doctor promptly. These symptoms may be serious.

Ask a doctor before use if you have

- persistent or chronic cough such as occurs with smoking, asthma or emphysema
- cough accompanied by excessive phlegm (mucus)

When using this product do not exceed recommended usage

Stop use and ask doctor if

- cough persists for more than 7 days, or is accompanied by fever, rash, or persistent headache. These could be signs of a serious condition.
- sore throat is severe, or irritation, pain or redness lasts or worsens
- sore mouth does not improve in 7 days

PREGNANCY OR BREAST FEEDING

If pregnant or breast-feeding, ask a health professional before use.

Keep out of reach of children. In case of accidental overdose, get medical help or contact a Poison Control Center right away.

Directions

Adults and children 5 years and over: Allow 1 drop to dissolve slowly in mouth; may be repeated every 2 hours as necessary or as directed by doctor. Children under 5 years: Ask a doctor.

Other information

- 10 calories per cough drop
- store at room temperature
- protect from moisture and heat

Inactive ingredients

Artificial cherry flavor, corn syrup, eucalyptus oil, FD&C Red No. 40 and sucrose

Questions?

1-866-651-3660 Monday-Friday 8:00am-5:00pm EST

PRINCIPAL DISPLAY PANEL - 50 Lozenge Box

Product #1202

Cherry Flavored
Cough Drops

Active ingredient:
Menthol

Cough suppressant/Oral anesthetic

- Relieves coughs and soothes throats
- Pleasant tasting cherry flavored lozenge
- Menthol eucalyptus vapors ease congestion

50 Lozenges

PRINCIPAL DISPLAY PANEL - 100 Lozenge Box

Product #1204

Cherry Flavored
Cough Drops

Active ingredient:
Menthol

Cough suppressant/Oral anesthetic

- Relieves coughs and soothes throats
- Pleasant tasting cherry flavored lozenge
- Menthol eucalyptus vapors ease congestion

100 Lozenges